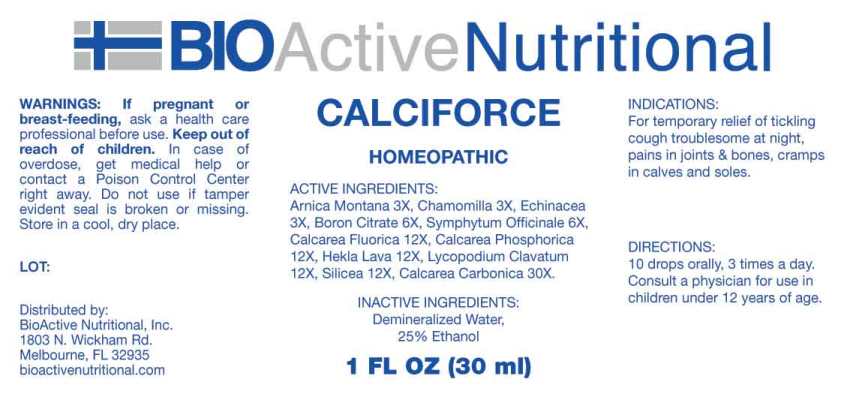 DRUG LABEL: Calciforce
NDC: 43857-0569 | Form: LIQUID
Manufacturer: BioActive Nutritional, Inc.
Category: homeopathic | Type: HUMAN OTC DRUG LABEL
Date: 20230607

ACTIVE INGREDIENTS: ARNICA MONTANA WHOLE 3 [hp_X]/1 mL; MATRICARIA CHAMOMILLA WHOLE 3 [hp_X]/1 mL; ECHINACEA ANGUSTIFOLIA WHOLE 3 [hp_X]/1 mL; BORON CITRATE 6 [hp_X]/1 mL; COMFREY ROOT 6 [hp_X]/1 mL; CALCIUM FLUORIDE 12 [hp_X]/1 mL; TRIBASIC CALCIUM PHOSPHATE 12 [hp_X]/1 mL; HEKLA LAVA 12 [hp_X]/1 mL; LYCOPODIUM CLAVATUM SPORE 12 [hp_X]/1 mL; SILICON DIOXIDE 12 [hp_X]/1 mL; OYSTER SHELL CALCIUM CARBONATE, CRUDE 30 [hp_X]/1 mL
INACTIVE INGREDIENTS: WATER; ALCOHOL

Drug Facts:

ACTIVE INGREDIENTS:

Arnica Montana 3X, Chamomilla 3X, Echinacea (Angustifolia) 3X, Boron Citrate 6X, Symphytum Officinale 6X, Calcarea Fluorica 12X, Calcarea Phosphorica 12X, Hekla Lava 12X, Lycopodium Clavatum 12X, Silicea 12X, Calcarea Carbonica 30X.

INDICATIONS:

For temporary relief of tickling cough troublesome at night, pains in joints & bones, cramps in calves and soles.

WARNINGS:

If pregnant or breast-feeding, ask a health care professional before use.

Keep out of reach of children. In case of overdose, get medical help or contact a Poison Control Center right away.

Do not use if tamper evident seal is broken or missing.

Store in cool, dry place.

Keep out of reach of children. In case of overdose, get medical help or contact a Poison Control Center right away.

DIRECTIONS:

10 drops orally, 3 times a day. Consult a physician for use in children under 12 years of age.

INDICATIONS:

For temporary relief of tickling cough troublesome at night, pains in joints & bones, cramps in calves and soles.

INACTIVE INGREDIENTS:

Demineralized Water, 25% Ethanol.

QUESTIONS:

Distributed by:
BioActive Nutritional, Inc.
1803 N. Wickham Rd.
Melbourne, FL 32935
bioactivenutritional.com

PACKAGE LABEL DISPLAY:

BIOActive Nutritional
CALCIFORCE
HOMEOPATHIC
1 FL OZ (30 ml)